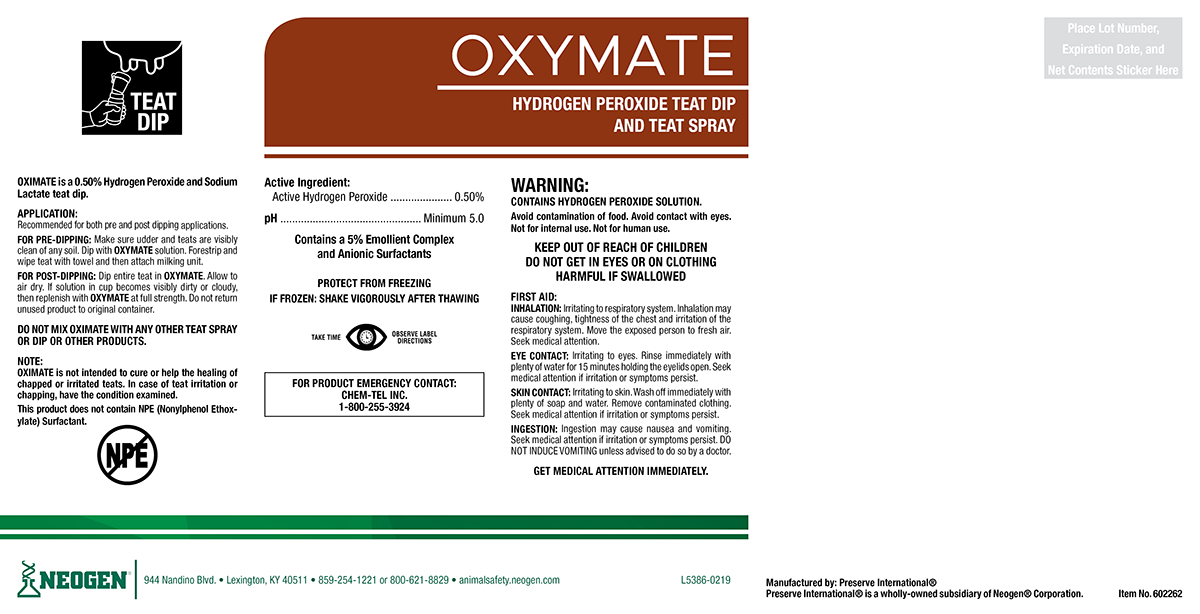 DRUG LABEL: Oxymate
NDC: 60648-9011 | Form: SOLUTION
Manufacturer: Preserve International
Category: animal | Type: OTC ANIMAL DRUG LABEL
Date: 20190517

ACTIVE INGREDIENTS: HYDROGEN PEROXIDE 5.95 g/1 L

OXYMATE

DOSAGE AND ADMINISTRATION

OXYMATE is a 0.5% hydrogen Peroxide and Sodium Lactate teat dip.

APPLICATION:

Recommended for both pre and post dipping applications.

FOR PRE-DIPPING: Make sure udder and teats are visibly clean of any soil. Dip with OXYMATE solution. Forestrip and wipe teat with towel and then attach milking unit.

FOR POST-DIPPING: Dip Entire teat in OXYMATE. Allow to air dry. If solution in cup becomes visibly dirty or cloudy, then replenish with OXYMATE at full strength. Do not return unused product to original container.

DO NOT MIX OXYMATE WITH ANY OTHER TEAT SPRAY OR DIP OR OTHER PRODUCTS.

NOTE:

OXYMATE is not intended to cure or help the healing of chapped or irritated teats. In case of teat irritation or chapping, have the condition examined.

This product does not contain NPE (Nonylphenol Ethoxylate) Surfactant.

WARNINGS AND PRECAUTIONS

PROTECT FROM FREEZING

IF FROZEN: SHAKE VIGOROUSLY AFTER THAWING

WARNINGS AND PRECAUTIONS

TAKE TIME OBSERVE LABEL DIRECTIONS

WARNING:

CONTAINS HYDROGEN PEROXIDE SOLUTION

Avoid contamination of food. Avoid contact with eyes. Not for internal use. Not for human use.

KEEP OUT OF REACH OF CHILDREN

DO NOT GET IN EYES OR ON CLOTHING

HARMFUL IF SWALLOWED

FIRST AID:

INHALATION: Irritating to respiratory system. Inhalation may cause coughing, lightness of the chest and irritation of the respiratory system. Move the exposed person to fresh air. Seek medical attention.

EYE CONTACT: Irritating to eyes. Rinse immediately with plenty of water for 15 minutes holding the eyelids open. Seek medical attention if irritation or symptoms persist.

SKIN CONTACT: Irritating to skin. Wash off immediately with plenty of soap and water. Remove contaminated clothing. Seek medical attention if irritation or symptoms persist.

INGESTION: Ingestion may cause nausea and vomiting. Seek medical attention if irritation or symptoms persist. DO NOT INDUCE VOMITING unless advised to do so by a doctor.
GET MEDICAL ATTENTION IMMEDIATELY.

FOR PRODUCT EMERGENCY CONTACT: Chem-Tel Inc. 1-800-255-3924

PACKAGE LABEL

OXYMATE

HYDROGEN PEROXIDE TEAT DIP AND TEAT SPRAY

Active Ingredients:

Active Hydrogen Peroxide..........0.50%
pH.....................................Minimum 5.00
Contains a 5% Emollient Complex and Anionic Surfactants

Manufactured By: Preserve International®

Preserve International® is a wholly-owned subsidiary of Neogen® Corporation.

NEOGEN®

944 Nandino Blvd.

Lexington, KY 40511

859-254-1221 or 800-621-8829

animalsafety.neogen.com